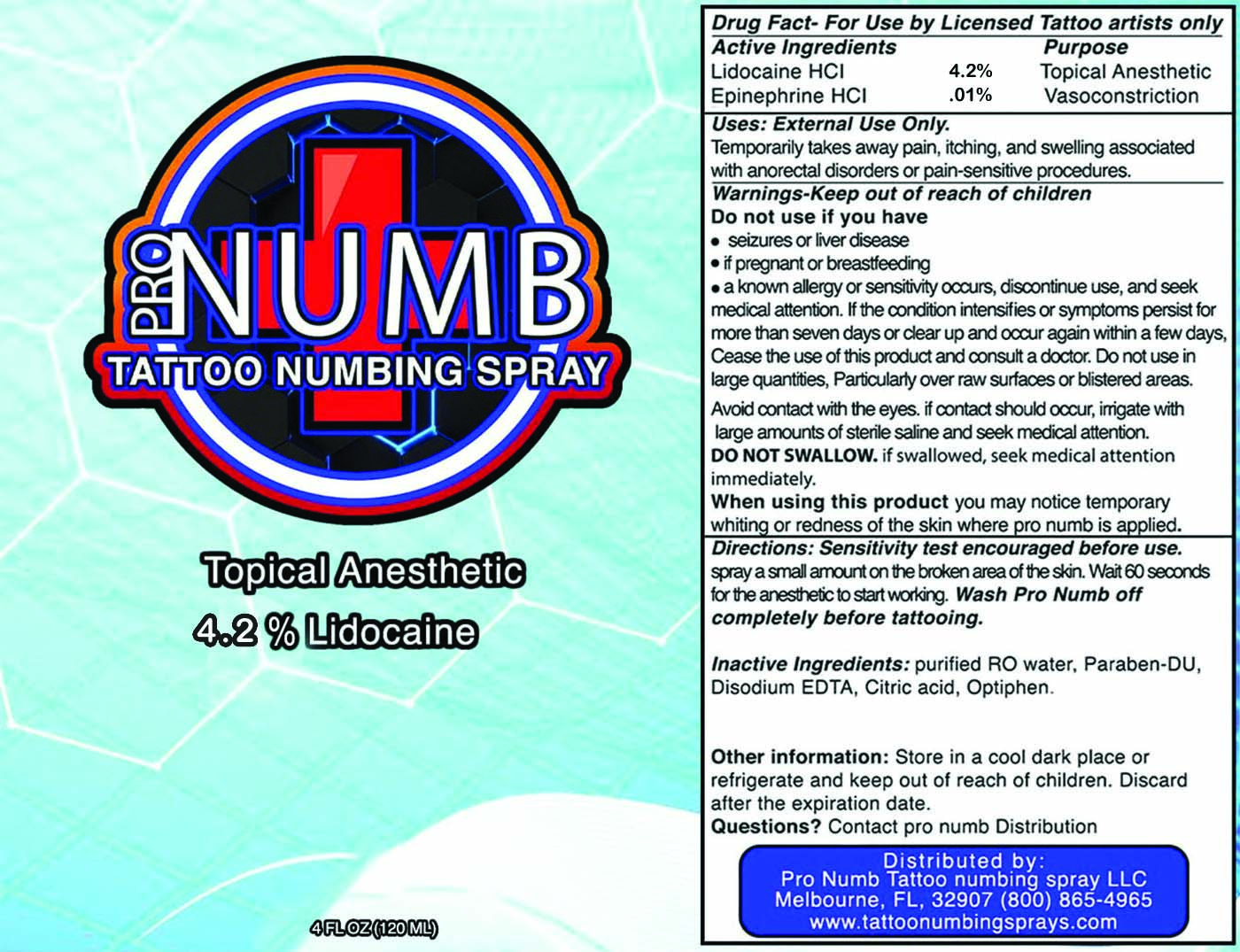 DRUG LABEL: Pro Numb Sensitive Skin
NDC: 83389-112 | Form: SPRAY
Manufacturer: Pro Numb Tattoo Numbing Spray LLC
Category: otc | Type: HUMAN OTC DRUG LABEL
Date: 20260202

ACTIVE INGREDIENTS: EPINEPHRINE HYDROCHLORIDE 0.1 mg/100 mL; LIDOCAINE HYDROCHLORIDE 4.2 mg/100 mL
INACTIVE INGREDIENTS: CAPRYLYL GLYCOL; PHENOXYETHANOL; CITRIC ACID MONOHYDRATE; WATER; EDETATE DISODIUM; PROPYLPARABEN

Pro Numb Tattoo Sensetive Skin Spray 120 mL

Active Ingredient(s)

Lidocaine HCI 4.2% Epinephrine HCI .01%

Purpose

Topical Anesthetic
Vasoconstriction

Use

Temporarily takes away pain, itching, and swelling associated with anorectal disorders or pain-sensitive procedures.

Warnings

External Use Only. Keep out of reach of children.

Do not use if you have • seizures or liver disease • if pregnant or breastfeeding • a known allergy or sensitivity occurs, discontinue use, and seek medical attention. If the condition intensifies or symptoms persist for more than seven days or clear up and occur again within a few days, Cease the use of this product and consult a doctor. Do not use in large quantities, Particularly over raw surfaces or blistered areas. Avoid contact with the eyes. If contact should occur, irrigate with large amounts of sterile saline and seek medical attention. Do not swallow, if swallowed, seek medical attention immediately.

When using this product, you may notice temporary whiting or redness of the skin where Pro Numb is applied.

Keep out of reach of children.

Directions

A sensitivity test is encouraged before using. Spray a small amount on the broken area of the skin. Wait 60 seconds for the anesthetic to start working. Wash Pro Numb off completely before tattooing.

Other information

Store in a cool dark place or refrigerate and keep out of reach of children. Discard the item after the expiration date is due.

Inactive ingredients

Purified RO water, Paraben-DU, Disodium EDTA, Citric acid, Optiphen.

QUESTIONS

Contact Pro Numb Distribution. (800) 865-4965